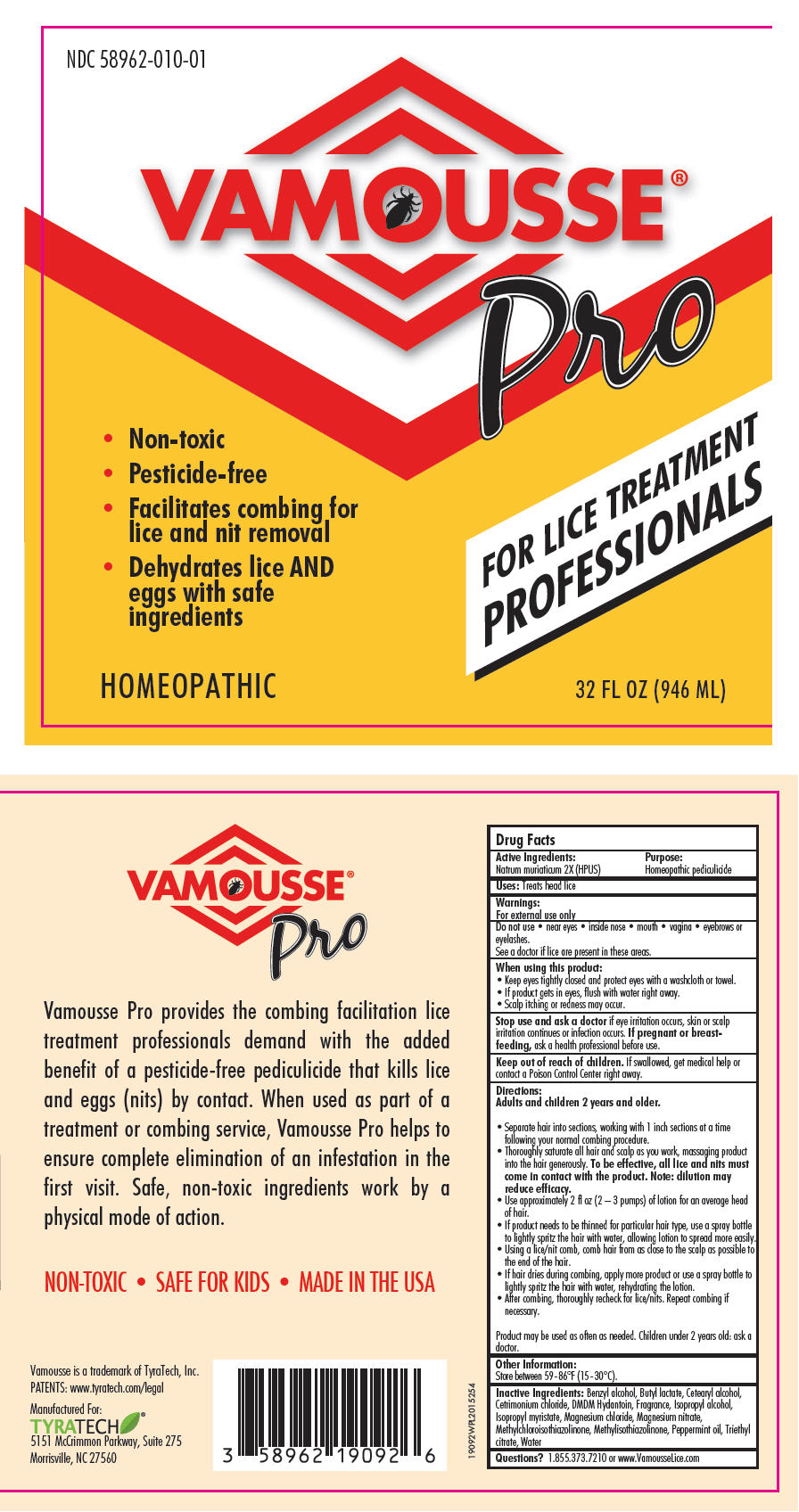 DRUG LABEL: Vamousse Pro Lice Treatment
NDC: 58962-010 | Form: LIQUID
Manufacturer: Tyra Tech, Inc.
Category: homeopathic | Type: HUMAN OTC DRUG LABEL
Date: 20150929

ACTIVE INGREDIENTS: SODIUM CHLORIDE 2 [hp_X]/1 mL
INACTIVE INGREDIENTS: BENZYL ALCOHOL; BUTYL LACTATE; CETOSTEARYL ALCOHOL; CETRIMONIUM CHLORIDE; DMDM HYDANTOIN; GERANIOL; ISOPROPYL ALCOHOL; ISOPROPYL MYRISTATE; MAGNESIUM CHLORIDE; MAGNESIUM NITRATE; METHYLCHLOROISOTHIAZOLINONE; METHYLISOTHIAZOLINONE; PEPPERMINT OIL; TRIETHYL CITRATE; WATER

Vamousse® Pro Lice Treatment

Drug Facts

Active Ingredients

Natrum muriaticum 2X (HPUS)

Purpose

Homeopathic pediculicide

Uses

Treats head lice

Warnings

For external use only

Do not use

- near eyes
- inside nose
- mouth
- vagina
- eyebrows or eyelashes.

See a doctor if lice are present in these areas.

When using this product:

- Keep eyes tightly closed and protect eyes with a washcloth or towel.
- If product gets in eyes, flush with water right away.
- Scalp itching or redness may occur.

Stop use and ask a doctor if eye irritation occurs, skin or scalp irritation continues or infection occurs. If pregnant or breastfeeding, ask a health professional before use.

Keep out of reach of children. If swallowed, get medical help or contact a Poison Control Center right away.

Directions

Adults and children 2 years and older.

- Separate hair into sections, working with 1 inch sections at a time following your normal combing procedure.
- Thoroughly saturate all hair and scalp as you work, massaging product into the hair generously. To be effective, all lice and nits must come in contact with the product. Note: dilution may reduce efficacy.
- Use approximately 2 fl oz (2 – 3 pumps) of lotion for an average head of hair.
- If product needs to be thinned for particular hair type, use a spray bottle to lightly spritz the hair with water, allowing lotion to spread more easily.
- Using a lice/nit comb, comb hair from as close to the scalp as possible to the end of the hair.
- If hair dries during combing, apply more product or use a spray bottle to lightly spritz the hair with water, rehydrating the lotion.
- After combing, thoroughly recheck for lice/nits. Repeat combing if necessary.

Product may be used as often as needed. Children under 2 years old: ask a doctor.

Other Information

Store between 59-86°F (15 -30°C).

Inactive Ingredients

Benzyl alcohol, Butyl lactate, Cetearyl alcohol, Cetrimonium chloride, DMDM Hydantoin, Fragrance, Isopropyl alcohol, Isopropyl myristate, Magnesium chloride, Magnesium nitrate, Methylchloroisothiazolinone, Methylisothiazolinone, Peppermint oil, Triethyl citrate, Water

Questions?

1.855.373.7210 or www.VamousseLice.com

PRINCIPAL DISPLAY PANEL - 946 ML Bottle Label

NDC 58962-010-01

VAMOUSSE®

Pro

- Non-toxic
- Pesticide-free
- Facilitates combing for
  lice and nit removal
- Dehydrates lice AND
  eggs with safe
  ingredients

FOR LICE TREATMENT
PROFESSIONALS

HOMEOPATHIC
32 FL OZ (946 ML)